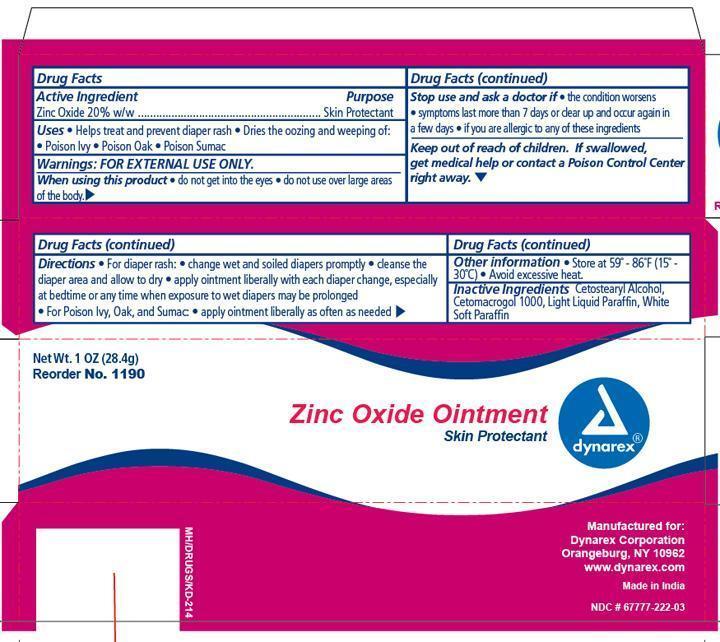 DRUG LABEL: Zinc Oxide
NDC: 67777-222 | Form: OINTMENT
Manufacturer: Dynarex Corporation
Category: otc | Type: HUMAN OTC DRUG LABEL
Date: 20170405

ACTIVE INGREDIENTS: ZINC OXIDE 200 mg/1 g
INACTIVE INGREDIENTS: CETOSTEARYL ALCOHOL; CETETH-20; LIGHT MINERAL OIL; PETROLATUM

Zinc Oxide Ointment

ACTIVE INGREDIENT

Section Text

Active Ingredient Purpose

Zinc Oxide (200mg in each gram) Skin Protectant

Purpose:

- Helps treat and prevent diaper rash.

- Dries the oozing and weeping of;
- poison ivy
- poison oak
- poison sumac

Warnings:

For External Use Only

When using this product:

- Do not get in eyes.

Stop use and ask a doctor if:

- conditions worsens
- symptoms last more than 7 days or clear up and occur again in a few days, consult a physician.
- over large areas of the body
- if you are allergic to any of these ingredients

Do not use on:

- deep or puncture wounds
- animal bites
- serious burns

Keep out of reach of children. If swallowed, get medical help or contact a Poison Control Center right away.

Directions:

For diaper rash:

- change wet and soiled diapers promptly
- cleanse the diaper area and allow to dry
- apply ointment liberally with each diaper change, especially at bedtime or anytime when exposure to wet diapers may be prolonged

For poison ivy, poison oak, poison sumac:

- apply liberally as often as needed

Inactive Ingredients

Cetostearyl alcohol, Cetomacrogal 1000, Light Liquid Paraffin, White Soft Paraffin

Principal Display

zinc.jpg